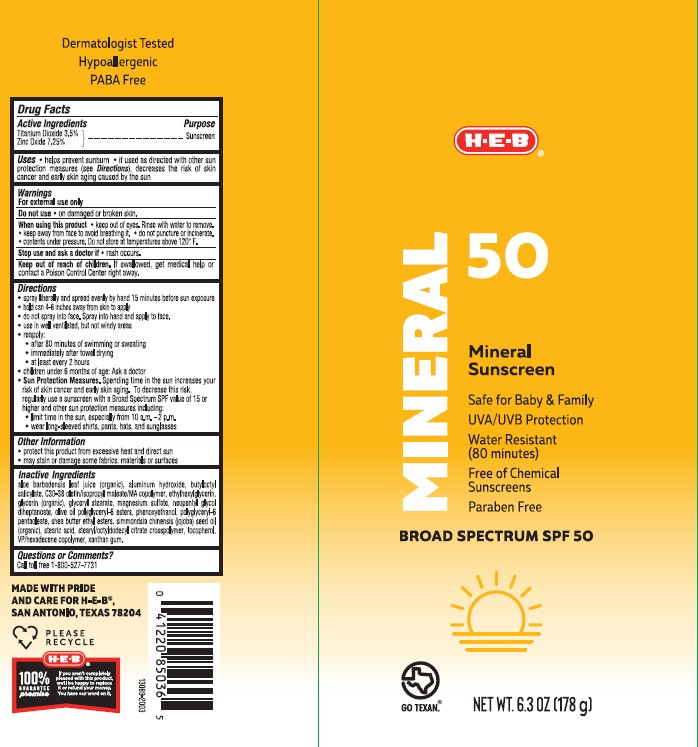 DRUG LABEL: H.E.B. Mineral Sunscreen Broad Spectrum SPF 50
NDC: 37808-295 | Form: SPRAY
Manufacturer: H.E.B.
Category: otc | Type: HUMAN OTC DRUG LABEL
Date: 20241015

ACTIVE INGREDIENTS: TITANIUM DIOXIDE 35 mg/1 g; ZINC OXIDE 72.5 mg/1 g
INACTIVE INGREDIENTS: STEARIC ACID; MAGNESIUM SULFATE HEPTAHYDRATE; .ALPHA.-TOCOPHEROL, DL-; OLIVE OIL POLYGLYCERYL-6 ESTERS; VINYLPYRROLIDONE/HEXADECENE COPOLYMER; ALOE VERA LEAF; GLYCERIN; XANTHAN GUM; BUTYLOCTYL SALICYLATE; NEOPENTYL GLYCOL DIHEPTANOATE; STEARYL/OCTYLDODECYL CITRATE CROSSPOLYMER; GLYCERYL 1-STEARATE; JOJOBA OIL; SHEA BUTTER ETHYL ESTERS; ALUMINUM HYDROXIDE; PHENOXYETHANOL; ETHYLHEXYLGLYCERIN

H.E.B. Mineral Sunscreen Broad Spectrum SPF 50 Continuous Spray

Active ingredients

Titanium Dioxide 3.5%

Zinc Oxide 7.25%

Purpose

Sunscreen

Uses

- helps prevent sunburn
- if used as directed with other sun protection measures (see Directions), decreases the risk of skin cancer and early skin aging caused by the sun

Warnings

For external use only

FLAMMABLE:

• do not use near heat, flame or while smoking
• avoid long term storage above 104°F (40°C)

Do not use

- on damaged or broken skin

When using this product

• keep out of eyes. Rinse with water to remove.

• keep away from to avoid breathing it.

• do not puncture or incinerate. Contents under pressure.

• do not store at temperatures above 120° F.

Stop use and ask doctor if

- rash occurs.

Keep out of reach of children.

If product is swallowed, get medical help or contact a Poison Control Center right away.

Directions

• spray liberally and spread evenly by hand 15 minutes before sun exposure
• hold can 4-6 inches away from skin top apply
• do not spray into face. Spray into hand and apply to face.
• use in a well ventilated areas
reapply:
• after 80 minutes of swimming or sweating
• immediately after towel drying
• at least every 2 hours

• children under 6 months: Ask a doctor
• Sun Protection Measures. Spending time in the sun increases your risk of skin cancer and early skin aging. To decrease this risk, regularly use a sunscreen with a Broad Spectrum SPF Value of 15 or higher and other sun protection measures including:
• limit time in the sun, especially from 10 a.m. - 2 p.m.
• wear long-sleeved shirts, pants, hats, and sunglasses

Other Information

• protect the product in the container from excessive heat and direct sun
• may stain or damage some fabrics

Inactive ingredients

Aloe Barbadensis Leaf Juice, Shea Butter Ethyl Esters, Neopentyl Glycol Diheptanoate,Butyloctyl Salicylate, Simmondsia Chinensis (Jojoba) Seed Oil, Olive Oil, Polyglyceryl-6 Esters, Polyglyceryl-6 Pentaoleate, Phenoxyethanol, Stearyl/Octyldodecyl Citrate Crosspolymer, C30-38 Olefin/Isopropyl Maleate/MA Copolymer, VP/Hexadecene Copolymer, Glycerin, Aluminum Hydroxide, Stearic Acid,Magnesium Sulfate, Glyceryl Stearate,Xanthan Gum, Ethylhexylglycerin,Tocopherol

Label

H.E.B. Mineral Sunscreen Broad Spectrum SPF 50 Continuous Spray

6.3 oz (178 g)